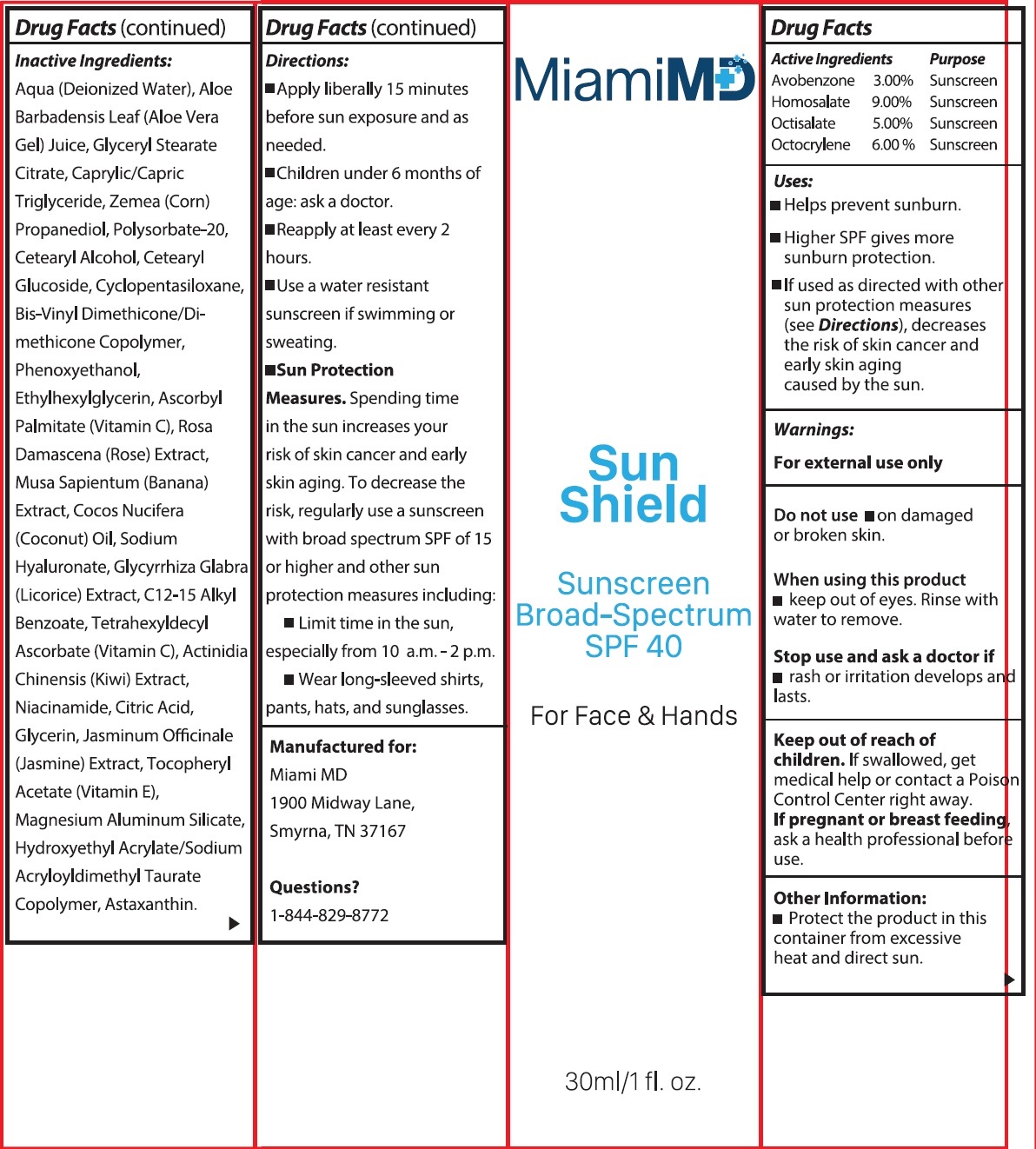 DRUG LABEL: MIAMI MD SUN SHIELD Broad Spectrum SPF 40
NDC: 83140-373 | Form: CREAM
Manufacturer: BRAND BOLT LLC
Category: otc | Type: HUMAN OTC DRUG LABEL
Date: 20231106

ACTIVE INGREDIENTS: AVOBENZONE 30 mg/1 mL; HOMOSALATE 90 mg/1 mL; OCTISALATE 50 mg/1 mL; OCTOCRYLENE 60 mg/1 mL
INACTIVE INGREDIENTS: WATER; ALOE VERA LEAF; MEDIUM-CHAIN TRIGLYCERIDES; CORN; POLYSORBATE 20; CETOSTEARYL ALCOHOL; CETEARYL GLUCOSIDE; CYCLOMETHICONE 5; PHENOXYETHANOL; ETHYLHEXYLGLYCERIN; ASCORBYL PALMITATE; BANANA; COCONUT OIL; HYALURONATE SODIUM; GLYCYRRHIZA GLABRA; ALKYL (C12-15) BENZOATE; TETRAHEXYLDECYL ASCORBATE; KIWI FRUIT; NIACINAMIDE; CITRIC ACID MONOHYDRATE; GLYCERIN; JASMINUM OFFICINALE FLOWER; .ALPHA.-TOCOPHEROL ACETATE; MAGNESIUM ALUMINUM SILICATE; ASTAXANTHIN

MIAMI MD SUN SHIELD Broad Spectrum SPF 40

Active Ingredients

Avobenzone 3.00% Homosalate 9.00% Octisalate 5.00% Octocrylene 6.00%

Purpose

Sunscreen

Uses:

- Helps prevent sunburn.
- Higher SPF gives more sunburn protection.
- If used as directed with other sun protection measures (see), decreases the risk of skin cancer and early skin aging caused by the sun. Directions

Warnings

For external use only

Do not use

- on damaged or broken skin.

When using this product

keep out of eyes. Rinse with water to remove.

Stop use and ask a doctor if

rash or irritation develops and lasts.

Keep out of reach of children.

If swallowed, get medical help or contact a Poison Control Center right away.

If pregnant or breast feeding,

ask a health professional before use.

Other Information:

- Protect the product in this container from excessive heat and direct sun.

Inactive Ingredients:

Aqua (Deionized Water), Aloe Barbadensis Leaf (Aloe Vera Gel) Juice, Glyceryl Stearate Citrate, Caprylic/Capric Triglyceride, Zemea (Corn) Propanediol, Polysorbate-20, Cetearyl Alcohol, Cetearyl Glucoside, Cyclopentasiloxane, Bis-Vinyl Dimethicone/Dimethicone Copolymer, Phenoxyethanol, Ethylhexylglycerin, Ascorbyl Palmitate (Vitamin C), Rosa Damascena (Rose) Extract, Musa Sapientum (Banana) Extract, Cocos Nucifera (Coconut) Oil, Sodium Hyaluronate, Glycyrrhiza Glabra (Licorice) Extract, C12-15 Alkyl Benzoate, Tetrahexyldecyl Ascorbate (Vitamin C), Actinidia Chinensis (Kiwi) Extract, Niacinamide, Citric Acid, Glycerin, Jasminum Officinale (Jasmine) Extract, Tocopheryl Acetate (Vitamin E), Magnesium Aluminum Silicate, Hydroxyethyl Acrylate/Sodium Acryloyldimethyl Taurate Copolymer, Astaxanthin.

Directions

- Apply liberally 15 minutes before sun exposure and as needed.
- Children under 6 months of age: ask a doctor.
- Reapply at least every 2 hours.
- Use a water resistant sunscreen if swimming or sweating.
- Spending time in the sun increases your risk of skin cancer and early skin aging. To decrease the risk, regularly use a sunscreen with broad spectrum SPF of 15 or higher and other sun protection measures including: Sun Protection Measures.
- Limit time in the sunm especially from 10 a.m. - 2 p.m.
- Wear long-sleeved shirts, pants, hats, and sunglasses.

Questions?

1-844-829-8772